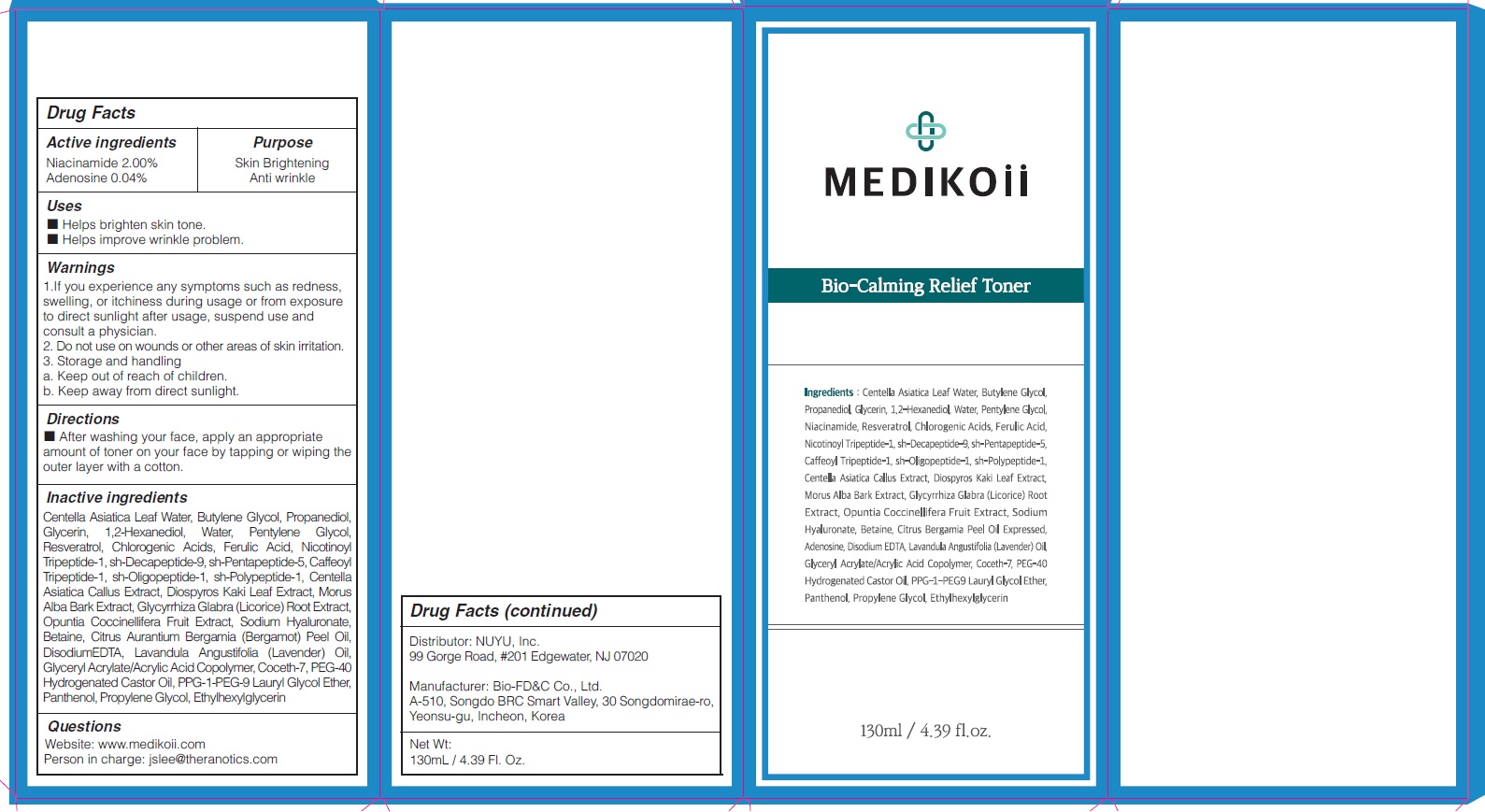 DRUG LABEL: MEDIKOii Bio Calming Relief Toner
NDC: 72695-0012 | Form: LIQUID
Manufacturer: THERANOTICS CO.,LTD.
Category: otc | Type: HUMAN OTC DRUG LABEL
Date: 20200529

ACTIVE INGREDIENTS: Niacinamide 2 g/100 mL; ADENOSINE 0.04 g/100 mL
INACTIVE INGREDIENTS: CENTELLA ASIATICA LEAF; Butylene Glycol; Propanediol

Drug Facts

ACTIVE INGREDIENTS

Niacinamide 2.00%
Adenosine 0.04%

INACTIVE INGREDIENTS

Centella Asiatica Leaf Water, Butylene Glycol, Propanediol, Glycerin, 1,2-Hexanediol, Water, Pentylene Glycol, Resveratrol, Chlorogenic Acids, Ferulic Acid, Nicotinoyl Tripeptide-1, sh-Decapeptide-9, sh-Pentapeptide-5, Caffeoyl Tripeptide-1, sh-Oligopeptide-1, sh-Polypeptide-1, Centella Asiatica Callus Extract, Diospyros Kaki Leaf Extract, Morus Alba Bark Extract, Glycyrrhiza Glabra (Licorice) Root Extract, Opuntia Coccinellifera Fruit Extract, Sodium Hyaluronate, Betaine, Citrus Aurantium Bergamia (Bergamot) Peel Oil, DisodiumEDTA, Lavandula Angustifolia (Lavender) Oil, Glyceryl Acrylate/Acrylic Acid Copolymer, Coceth-7, PEG-40 Hydrogenated Castor Oil,
PPG-1-PEG-9 Lauryl Glycol Ether, Panthenol, Propylene Glycol, Ethylhexylglycerin

PURPOSE

Skin Brightening
Anti wrinkle

WARNINGS

1.If you experience any symptoms such as redness, swelling, or itchiness during usage or from exposure to direct sunlight after usage, suspend use and consult a physician.
2. Do not use on wounds or other areas of skin irritation.
3. Storage and handling
a. Keep out of reach of children.
b. Keep away from direct sunlight.

KEEP OUT OF REACH OF CHILDREN

Uses

■ Helps brighten skin tone.
■ Helps improve wrinkle problem.

Directions

■ After washing your face, apply an appropriate amount of toner on your face by tapping or wiping the outer layer with a cotton.

QUESTIONS

Website: www.medikoii.com
Person in charge: jslee@theranotics.com